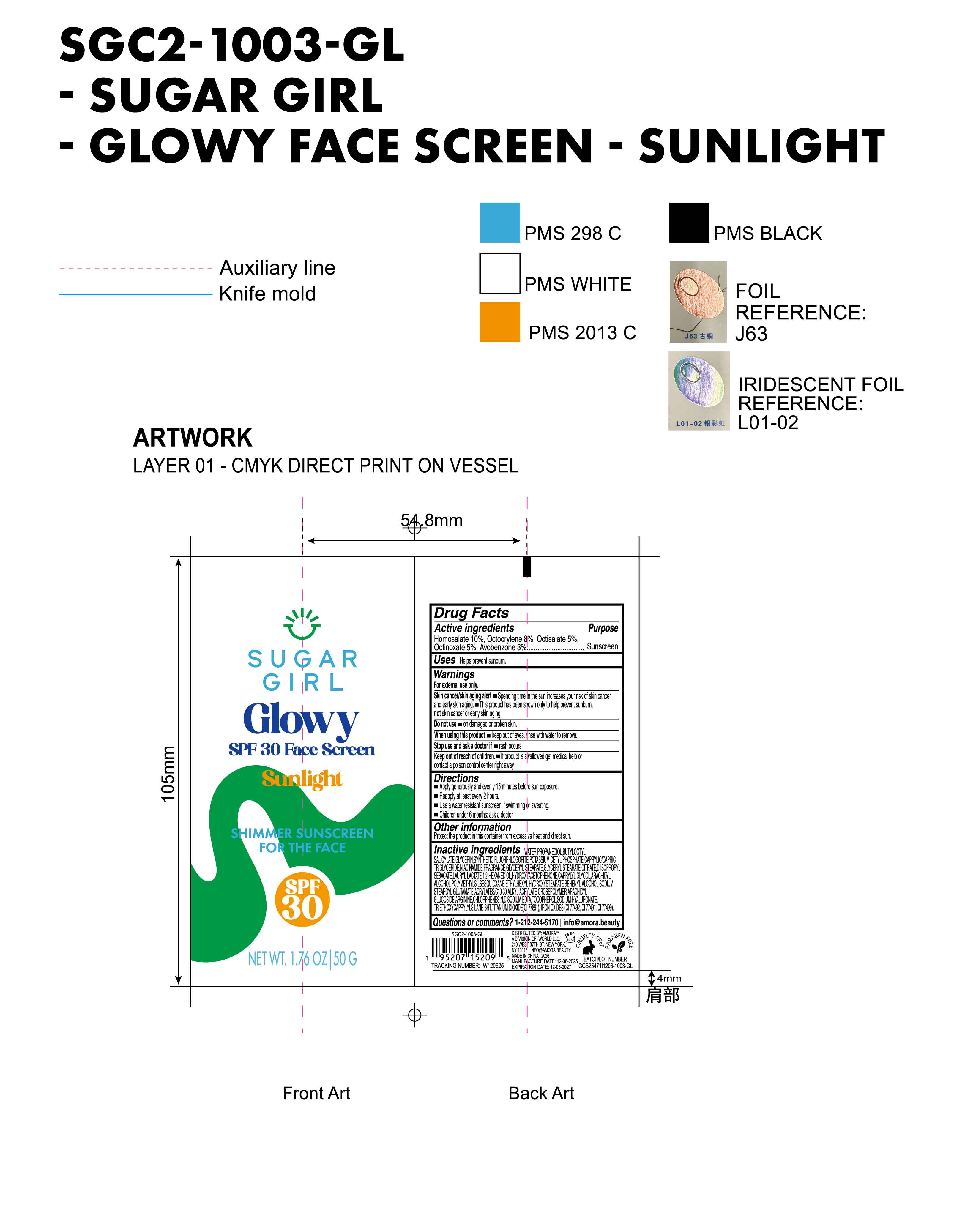 DRUG LABEL: Sugargirl Glowy SPF 30 Face Screen Sunlight Shimmer Sunscreen for the face
NDC: 85161-138 | Form: CREAM
Manufacturer: Longway Technology(Guangzhou)Co.,Ltd.
Category: otc | Type: HUMAN OTC DRUG LABEL
Date: 20251223

ACTIVE INGREDIENTS: HOMOSALATE 0.1 g/1 g; OCTINOXATE 0.05 g/1 g; OCTISALATE 0.05 g/1 g; OCTOCRYLENE 0.08 g/1 g; AVOBENZONE 0.03 g/1 g
INACTIVE INGREDIENTS: DIISOPROPYL SEBACATE; CHLORPHENESIN; CI 77499; TOCOPHEROL; PROPANEDIOL; ARACHIDYL GLUCOSIDE; ARGININE; GLYCERYL STEARATE CITRATE; FRAGRANCE 13576; BUTYLOCTYL SALICYLATE; SODIUM STEAROYL GLUTAMATE; ACRYLATES/C10-30 ALKYL ACRYLATE CROSSPOLYMER (60000 MPA.S); TRIETHOXYCAPRYLYLSILANE; NIACINAMIDE; GLYCERYL STEARATE; HYDROXYACETOPHENONE; CAPRYLYL GLYCOL; BHT; CI 77891; 1,2-HEXANEDIOL; SODIUM HYALURONATE; CI 77491; POTASSIUM CETYL PHOSPHATE; EDETATE DISODIUM; MAGNESIUM POTASSIUM ALUMINOSILICATE FLUORIDE; BEHENYL ALCOHOL; POLYMETHYLSILSESQUIOXANE (11 MICRONS); WATER; GLYCERIN; ETHYLHEXYL HYDROXYSTEARATE; CI 77492; LAURYL LACTATE; ARACHIDYL ALCOHOL; CAPRYLIC/CAPRIC TRIGLYCERIDE

ACTIVE INGREDIENT

Homosalate 10%,Octocrylene 8%, Octisalate 5%,Octinoxate 5%, Avobenzone 3%

INACTIVE INGREDIENT

WATER, PROPANEDIOL, BUTYLOCTYL SALICYLATE, GLYCERIN, SYNTHETIC FLUORPHLOGOPITE, POTASSIUM CETYL PHOSPHATE, CAPRYLIC/CAPRIC TRIGLYCERIDE, NIACINAMIDE, FRAGRANCE, GLYCERYL STEARATE, GLYCERYL STEARATE CITRATE, DIISOPROPYL SEBACATE, LAURYL LACTATE, 1,2-HEXANEDIOL, HYDROXYACETOPHENONE, CAPRYLYL GLYCOL, ARACHIDYL ALCOHOL, POLYMETHYLSILSESQUIOXANE, ETHYLHEXYL HYDROXYSTEARATE, BEHENYL ALCOHOL, SODIUM STEAROYL GLUTAMATE, ACRYLATES/C10-30 ALKYL ACRYLATE CROSSPOLYMER, ARACHIDYL GLUCOSIDE, ARGININE, CHLORPHENESIN, DISODIUM EDTA, TOCOPHEROL, SODIUM HYALURONATE, TRIETHOXYCAPRYLYLSILANE, BHT, TITANIUM DIOXIDE(CI 77891), IRON OXIDES（CI 77492, CI 77491 ,CI 77499）

INDICATIONS AND USAGE

Helps prevent sunburn

QUESTIONS

1-212-244-5170|info@amora.beauty

DOSAGE AND ADMINISTRATION

Apply generously and evenly 15 minutes befofe sun exposure.\

Reapply at least every 2 hours.

Use a water resistant sunscreen if swimming or sweating.
Children under 6 months: ask a doctor.

OTHER SAFETY INFORMATION

Protect the product in this container from excessive heat and direct sun.

KEEP OUT OF REACH OF CHILDREN

If product is swallowed get medical help or contact a poison control center right away

WARNINGS

For external use only.

Skin cancer/skin aging alert Spending time in the sun increases your risk of skin cancer and early skin aging.

This product has been shown only to help prevent sunburn,not skin cancer or early skin aging.

Do not use on damaged or broken skin.

When using this product keep out of eyes.rinse with water to remove.

Stop use and ask a doctor if rash occurs

Keep out of reach of children. .lf product is wallowed get medical help or contact a poison control center right away.

PURPOSE

Sunscreen